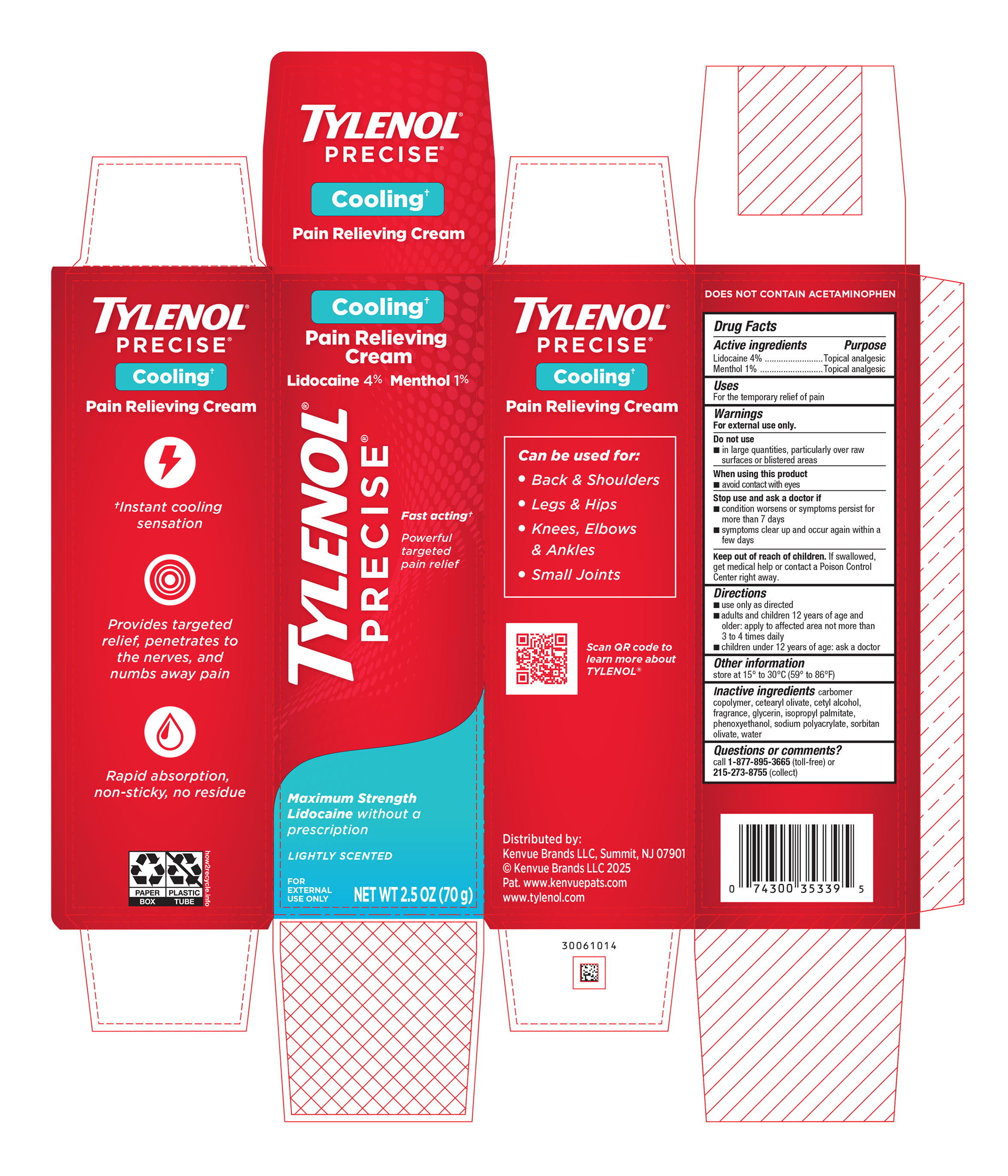 DRUG LABEL: Tylenol Precise Cooling Pain Relieving
NDC: 69968-0793 | Form: CREAM
Manufacturer: Kenvue Brands LLC
Category: otc | Type: HUMAN OTC DRUG LABEL
Date: 20260216

ACTIVE INGREDIENTS: MENTHOL, UNSPECIFIED FORM 10 mg/1 g; LIDOCAINE 40 mg/1 g
INACTIVE INGREDIENTS: CETEARYL OLIVATE; CETYL ALCOHOL; GLYCERIN; ISOPROPYL PALMITATE; PHENOXYETHANOL; WATER; SODIUM POLYACRYLATE (2500000 MW); SORBITAN OLIVATE

Tylenol Precise Cooling Pain Relieving Cream

Drug Facts

Active Ingredient

Lidocaine 4%............................................................................................... Topical analgesic

Menthol 1%.................................................................................................. Topical analgesic

Purpose

Topical analgesic

Uses

For the temporary relief of pain

Warnings

For external use only.

Do not use

▪ in large quantities, particularly over raw surfaces or blistered areas

When using this product

▪ avoid contact with eyes

Stop use and ask a doctor if

▪ condition worsens or symptoms persist for more than 7 days

▪ symptoms clear up and occur again within a few days

Keep out of reach of children. If swallowed, get medical help or contact a Poison Control Center right away.

Directions

- use only as directed
- adults and children 12 years of age and older: apply to affected area not more than 3 to 4 times daily
- children under 12 years of age: ask a doctor

Other Information

store at 15◦ to 30◦ C (59◦ to 86◦ F)

Inactive Ingredients

carbomer copolymer, cetearyl olivate, cetyl alcohol, fragrance, glycerin, isopropyl palmitate, phenoxyethanol, sodium polyacrylate, sorbitan olivate, water

Questions?

Call 1-877-895-3665 (toll-free) or 215- 273-8755 (collect)

Distributed by:

Kenvue Brands LLC
Summit, NJ 07901

PRINCIPAL DISPLAY PANEL - 70g Tube in carton Label

Cooling†

Pain Relieving

Cream

Lidocaine 4% Menthol 1%

TYLENOL®

PRECISE®

Fast acting†

Powerful

targeted

pain relief

Maximum Strength

Lidocaine without a

prescription

LIGHTLY SCENTED

FOR

EXTERNAL

USE ONLY

NET WT 2.5 OZ (70 g)